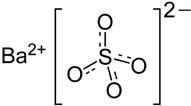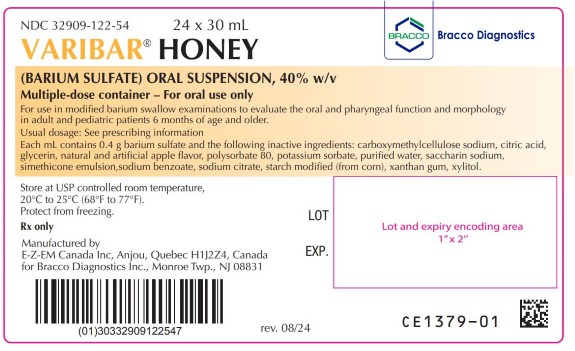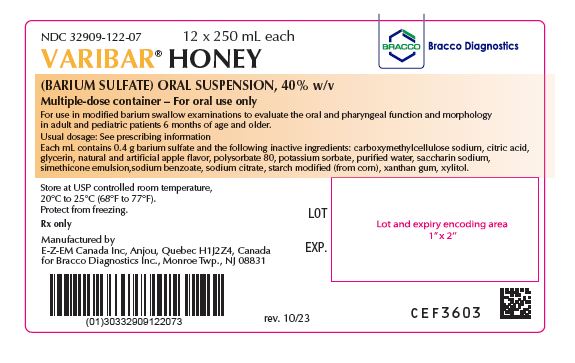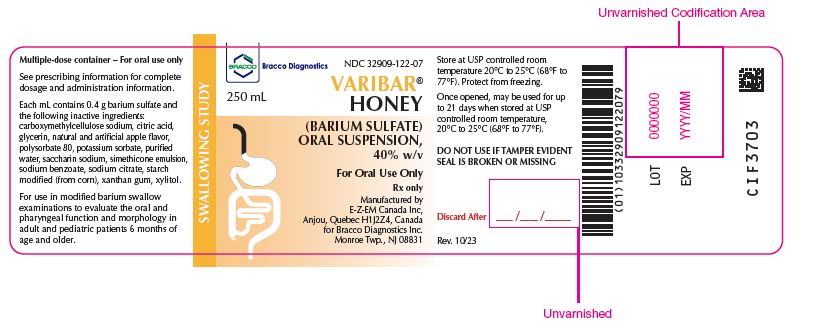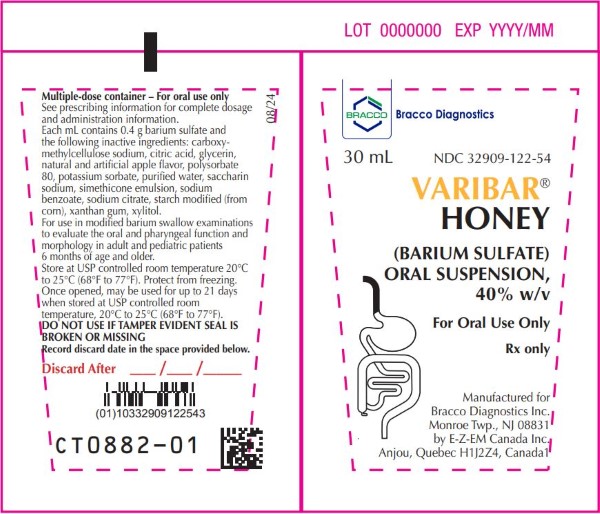 DRUG LABEL: Varibar Honey
NDC: 32909-122 | Form: SUSPENSION
Manufacturer: E-Z-EM Canada Inc
Category: prescription | Type: HUMAN PRESCRIPTION DRUG LABEL
Date: 20241107

ACTIVE INGREDIENTS: Barium Sulfate 400 mg/1 mL
INACTIVE INGREDIENTS: anhydrous citric acid; carboxymethylcellulose sodium; dimethicone 350; dimethicone 1000; glycerin; modified corn starch (1-octenyl succinic anhydride); polysorbate 80; potassium sorbate; saccharin sodium; silicon dioxide; sodium benzoate; trisodium citrate dihydrate; water; xanthan gum; xylitol

HIGHLIGHTS OF PRESCRIBING INFORMATION

These highlights do not include all the information needed to use VARIBAR HONEY safely and effectively. See full prescribing information for VARIBAR HONEY.
VARIBAR HONEY (barium sulfate) oral suspension
Initial U.S. Approval: 2016

1 INDICATIONS AND USAGE

VARIBAR HONEY is a radiopaque contrast agent indicated for use in modified barium swallow examinations to evaluate the oral and pharyngeal function and morphology in adult and pediatric patients 6 months of age and older (1)

2 Dosage and administration

For oral use only – administer by syringe or spoon. The recommended dose is:

- Adults: 5 mL
- Pediatric patients: 1 to 3 mL
- During a single modified barium swallow examination, multiple doses may be administered
- Maximum cumulative dose: 30 mL (2)

3 DOSAGE FORMS AND STRENGTHS

Oral Suspension: barium sulfate (40% w/v) supplied in a multiple-dose bottle or tube for oral administration (3)

4 CONTRAINDICATIONS

- Known or suspected perforation of the gastrointestinal (GI) tract (4)
- Known obstruction of the GI tract (4)
- Conditions associated with high risk of GI perforation or aspiration (4)
- Known hypersensitivity to barium sulfate or any of the excipients of VARIBAR HONEY (4)

5 WARNINGS AND PRECAUTIONS

Hypersensitivity reactions: Emergency equipment and trained personnel should be immediately available (5.1)

- Intra-abdominal leakage: May occur in conditions such as GI fistula, ulcer, inflammatory bowel disease, appendicitis or diverticulitis, severe stenosis or obstructing lesions of the GI tract (5.2)
- Delayed GI transit and obstruction: Patients should maintain adequate hydration in days following barium sulfate procedure to avoid obstruction or impaction (5.3)
- Aspiration pneumonitis: Aspiration may occur during the modified barium swallow examination, monitor the patient for aspiration (5.4)

6 ADVERSE REACTIONS

Common adverse reactions include nausea, vomiting, diarrhea and abdominal cramping (6)

To report SUSPECTED ADVERSE REACTIONS, contact Bracco Diagnostics Inc at 1-800-257-5181 or FDA at 1-800-FDA-1088 or www.fda.gov/medwatch.

FULL PRESCRIBING INFORMATION

1 INDICATIONS AND USAGE

VARIBAR HONEY is indicated for modified barium swallow examinations to evaluate the oral and pharyngeal function and morphology in adult and pediatric patients 6 months of age and older.

2 Dosage and administration

2.1 Recommended Dosing

- The recommended dose of VARIBAR HONEY administered orally by syringe, spoon, or cup is:
  - Adults: 5 mL
  - Pediatric patients 6 months of age and older: 1 to 3 mL
- During a single modified barium swallow examination, multiple doses of VARIBAR HONEY may be administered, to assess the patient during multiple swallows and different radiographic views.
- The maximum cumulative dose is 30 mL.
- Once opened, write the discard after date on the immediate container label. Discard any unused product after 21 days.

2.2 Administration Instructions

- For oral use only
- Advise patients to hydrate following the barium sulfate procedure.

3 DOSAGE FORMS AND STRENGTHS

Oral suspension: barium sulfate (40% w/v) supplied in a multiple-dose plastic bottle or tube as a ready-to-use suspension for oral administration. Each bottle contains 250 mL of suspension; each tube contains 30 mL of suspension.

4 CONTRAINDICATIONS

VARIBAR HONEY is contraindicated in patients with:

- known or suspected perforation of the gastrointestinal (GI) tract
- known obstruction of the GI tract
- high risk of GI perforation such as those with a recent GI perforation, acute GI hemorrhage or ischemia, toxic megacolon, severe ileus, post GI surgery or biopsy, acute GI injury or burn, or recent radiotherapy to the pelvis
- high risk of aspiration such as those with known or suspected tracheo-esophageal fistula or obtundation
- known severe hypersensitivity to barium sulfate or any of the excipients of VARIBAR HONEY

5 WARNINGS AND PRECAUTIONS

5.1 Hypersensitivity Reactions

Barium sulfate preparations contain a number of excipients, including natural and artificial flavors and may induce serious hypersensitivity reactions. The manifestations include hypotension, bronchospasm and other respiratory impairments, and dermal reactions including rashes, urticaria and itching. A history of bronchial asthma, atopy, food allergies, or a previous reaction to a contrast agent may increase the risk for hypersensitivity reactions. Emergency equipment and trained personnel should be immediately available for treatment of a hypersensitivity reaction.

5.2 Intra-abdominal Barium Leakage

The use of VARIBAR HONEY is contraindicated in patients at high risk of perforation of the GI tract [see Contraindications (4)]. Administration of VARIBAR HONEY may result in leakage of barium from the GI tract in the presence of conditions such as carcinomas, GI fistula, inflammatory bowel disease, gastric or duodenal ulcer, appendicitis, or diverticulitis, and in patients with a severe stenosis at any level of the GI tract, especially if it is distal to the stomach. The barium leakage has been associated with peritonitis and granuloma formation.

5.3 Delayed Gastrointestinal Transit and Obstruction

Orally administered barium sulfate may accumulate proximal to a constricting lesion of the colon, causing obstruction or impaction with development of baroliths (inspissated barium associated with feces) and may lead to abdominal pain, appendicitis, bowel obstruction, or rarely perforation. Patients with the following conditions are at higher risk for developing obstruction or baroliths: severe stenosis at any level of the GI tract, impaired GI motility, electrolyte imbalance, dehydration, on a low residue diet, taking medications that delay GI motility, constipation, pediatric patients with cystic fibrosis or Hirschsprung disease, and the elderly [see Use in Specific Populations (8.4, 8.5)]. To reduce the risk of delayed GI transit and obstruction, patients should maintain adequate hydration after the barium sulfate procedure.

5.4 Aspiration Pneumonitis

The use of VARIBAR HONEY is contraindicated in patients with trachea-esophageal fistula [see Contraindications (4)]. Oral administration of barium is associated with aspiration pneumonitis, especially in patients with a history of food aspiration or with compromised swallowing mechanism. Vomiting following oral administration of barium sulfate may lead to aspiration pneumonitis.

In patients at risk for aspiration, begin the procedure with a small ingested volume of VARIBAR HONEY. Monitor the patient closely for aspiration, discontinue administration of VARIBAR HONEY if aspiration is suspected, and monitor for development of aspiration pneumonitis.

5.5 Systemic Embolization

Barium sulfate products may occasionally intravasate into the venous drainage of the GI tract and enter the circulation as a "barium embolus" leading to potentially fatal complications which include systemic and pulmonary embolism, disseminated intravascular coagulation, septicemia and prolonged severe hypotension. Although this complication is exceedingly uncommon after oral administration of a barium sulfate suspension, monitor patients for potential intravasation when administering barium sulfate.

6 ADVERSE REACTIONS

The following adverse reactions have been identified from spontaneous reporting or clinical studies of barium sulfate administered orally. Because the reactions are reported voluntarily from a population of uncertain size, it is not always possible to reliably estimate their frequency or to establish a causal relationship to drug exposure:

- Nausea, vomiting, diarrhea and abdominal cramping
- Serious adverse reactions and fatalities include aspiration pneumonitis, barium sulfate impaction, intestinal perforation with consequent peritonitis and granuloma formation, vasovagal and syncopal episodes

8 USE IN SPECIFIC POPULATIONS

8.1 Pregnancy

Risk Summary

VARIBAR HONEY is not absorbed systemically following oral administration, and maternal use is not expected to result in fetal exposure to the drug.

8.2 Lactation

Risk Summary

VARIBAR HONEY is not absorbed systemically by the mother following oral administration, and breastfeeding is not expected to result in exposure of the infant to the drug.

8.4 Pediatric Use

The efficacy of VARIBAR HONEY in pediatric patients above 6 months of age is based on successful opacification of the pharynx during modified barium swallow examinations [see Clinical Pharmacology (12.1)]. Safety and dosing recommendations in pediatric patients above 6 months of age are based on clinical experience.

VARIBAR HONEY is contraindicated in pediatric patients with trachea-esophageal fistula [see Contraindications (4)]. Pediatric patients with a history of asthma or food allergies may be at increased risk for development of hypersensitivity reactions [see Warnings and Precautions (5. 1)]. Monitor patients with cystic fibrosis or Hirschsprung disease for bowel obstruction after use [see Warnings and Precautions (5.3)].

8.5 Geriatric Use

Clinical studies of VARIBAR HONEY did not include sufficient numbers of subjects aged 65 and over to determine whether they respond differently from younger subjects. Other reported clinical experience has not identified differences in responses between the elderly and younger patients. In general, dose selection for an elderly patient should be cautious, usually starting at the low end of the dosing range, reflecting the greater frequency of decreased hepatic, renal, or cardiac function, and of concomitant disease or other drug therapy.

11 DESCRIPTION

VARIBAR HONEY (barium sulfate) is a radiographic contrast agent that is supplied as an off-white to lightly colored suspension (40% w/v) with an apple aroma for oral administration. The active ingredient barium sulfate is designated chemically as BaSO4 with a molecular weight of 233.4 g/mol, a density of 4.5 g/cm^3, and the following chemical structure:

VARIBAR HONEY has a viscosity of 3000 cPs and contains the following excipients: carboxymethylcellulose sodium, citric acid, glycerin, natural and artificial apple flavor, polysorbate 80, potassium sorbate, purified water, saccharin sodium, simethicone emulsion, sodium benzoate, sodium citrate, starch modified (from corn), xanthan gum, and xylitol.

12 CLINICAL PHARMACOLOGY

12.1 Mechanism of Action

Due to its high atomic number, barium (the active ingredient in VARIBAR HONEY) is opaque to x-rays and therefore acts as a positive contrast agent for radiographic studies.

12.2 Pharmacodynamics

Barium sulfate is biologically inert and has no known pharmacological effects.

12.3 Pharmacokinetics

Under physiological conditions, barium sulfate passes through the gastrointestinal tract in an unchanged form and is absorbed only in small, pharmacologically insignificant amounts.

13 NONCLINICAL TOXICOLOGY

13.1 Carcinogenesis, Mutagenesis, Impairment of Fertility

No animal studies have been performed to evaluate the carcinogenic potential of barium sulfate or potential effects on fertility.

16 HOW SUPPLIED/STORAGE AND HANDLING

16.1 How Supplied

VARIBAR HONEY is supplied as a suspension in both a multiple-dose polyethylene bottle containing 250 mL and multiple-dose polyethylene tube containing 30 mL of barium sulfate (40 % w/v).

Provided as: 12 x 250 mL bottles (NDC 32909-122-07); 24 x 30 mL tubes (NDC 32909-122-54)

16.2 Storage and Handling

Store at USP controlled room temperature 20°C to 25°C (68°F to 77°F). Protect from freezing.

Once opened, VARIBAR HONEY may be used for up to 21 days when stored at USP controlled room temperature, 20°C to 25°C (68°F to 77°F).

17 PATIENT COUNSELING INFORMATION

After administration, advise patients to:

- Maintain adequate hydration [see Dosage and Administration (2.2) and Warnings and Precautions (5.3)].
- Seek medical attention for worsening of constipation or slow gastrointestinal passage [see Warnings and Precautions (5.3)].
- Seek medical attention for any delayed onset of hypersensitivity: rash, urticaria, or respiratory difficulty [see Warnings and Precautions (5.1)].

Rx only

Manufactured by
EZEM Canada Inc
Anjou (Quebec) Canada H1J 2Z4

For
Bracco Diagnostics Inc.
Monroe Township, NJ 08831

VARIBAR is a registered trademark of E-Z-EM, Inc.

August 2024
CLF39-03

PACKAGE LABEL

250 mL Varibar® Honey - (Barium Sulfate) Oral Suspension Bottle
NDC: 32909-122-07

250 mL Varibar® Honey - (Barium Sulfate) Oral Suspension
NDC: 32909-122-07

30 mL Varibar® Honey - (Barium Sulfate) Oral Suspension Tube
NDC: 32909-122-54

30 mL Varibar® Honey - (Barium Sulfate) Oral Suspension
NDC: 32909-122-54